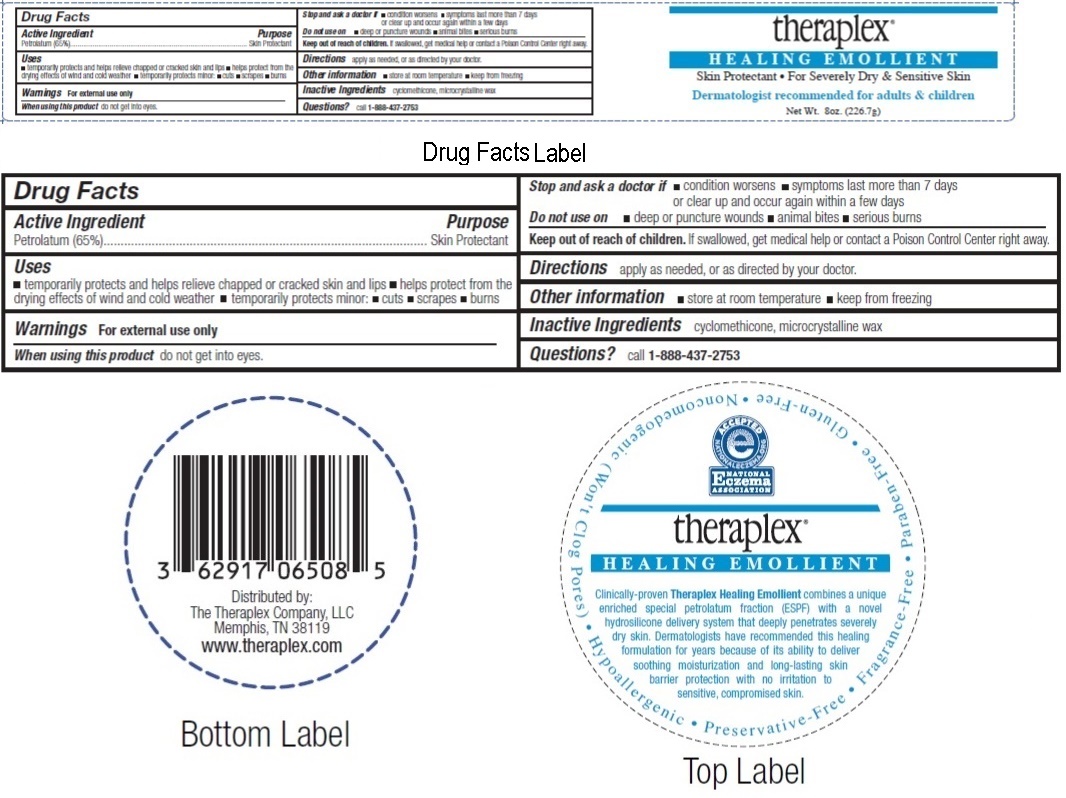 DRUG LABEL: Theraplex
NDC: 62917-065 | Form: CREAM
Manufacturer: The Theraplex Company, LLC
Category: otc | Type: HUMAN OTC DRUG LABEL
Date: 20170216

ACTIVE INGREDIENTS: PETROLATUM 65 g/100 g
INACTIVE INGREDIENTS: CYCLOMETHICONE; MICROCRYSTALLINE WAX

Theraplex Healing Emollient

Active Ingredient

Petrolatum (65%)

Purpose

Skin Protectant

Uses

• temporarily protects and helps relieve chapped or cracked skin and lips • helps protect from the drying effects of wind and cold weather • temporarily protects minor: • cuts • scrapes • burns

Warnings For external use only

When using this product do not get into eyes.

Stop and ask a doctor if • condition worsens • symptoms last more than 7 days or clear up and occur again within a few days

Do not use on • deep or puncture wounds • animal bites • serious burns

Keep out of reach of children. If swallowed, get medical help or contact a Poison Control Center right away.

DOSAGE AND ADMINISTRATION

Directions apply as needed, or as directed by your doctor.

Other information • store at room temperature • keep from freezing

Inactive Ingredients cyclomethicone, microcrystalline wax

Questions? call 1-888-437-2753

Clinically-proven Theraplex Healing Emollient combines a unique enriched special petrolatum fraction (ESPF) with a novel hydrosilicone delivery system that deeply penetrates severely dry skin. Dermatologists have recommended this healing formulation for years because of its ability to deliver soothing moisturization and long-lasting skin barrier protection with no irritation to sensitive, compromised skin.

- Noncomedogenic (Won't Clog Pores)
- Hypoallergenic
- Preservative-Free
- Fragrance-Free
- Paraben-Free
- Gluten-Free

Skin Protectant • For Severely Dry & Sensitive Skin
Dermatologist recommended for adults & children

Distributed by:
The Theraplex Company, LLC
Memphis, TN 38119
www.theraplex.com